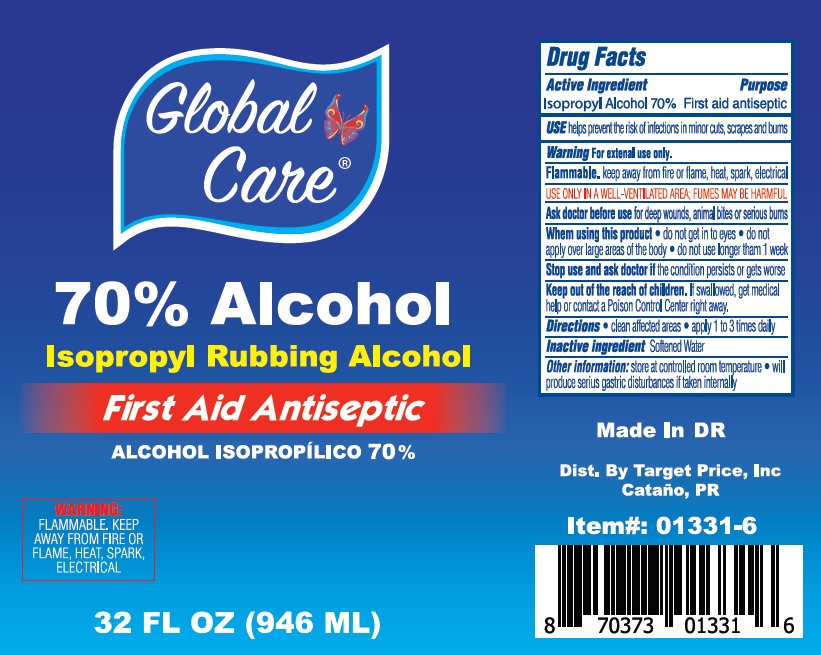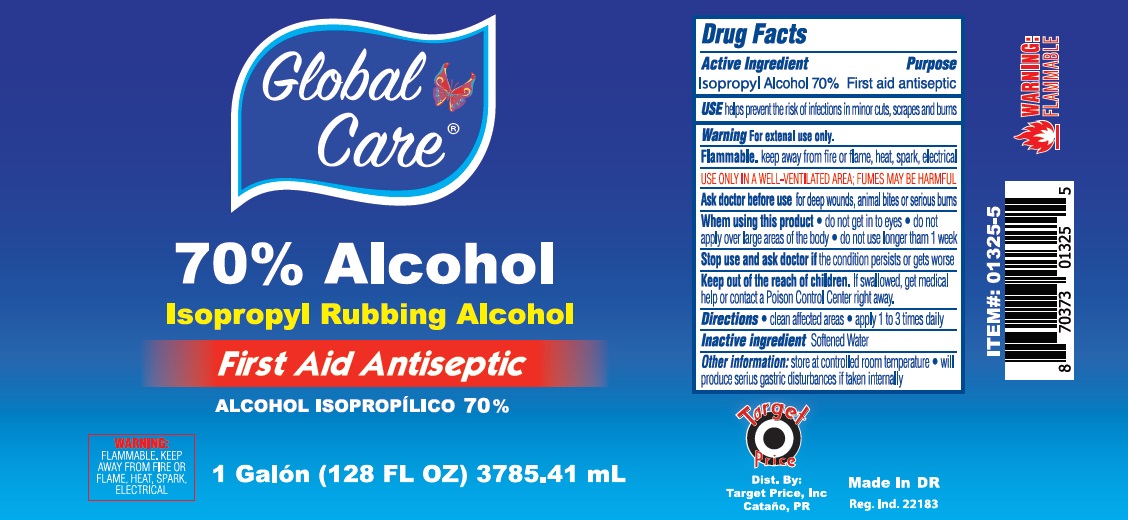 DRUG LABEL: Global Care Isopropyl Rubbing Alcohol
NDC: 72146-045 | Form: LIQUID
Manufacturer: Target Price Inc
Category: otc | Type: HUMAN OTC DRUG LABEL
Date: 20200915

ACTIVE INGREDIENTS: ISOPROPYL ALCOHOL 0.7 mL/1 mL
INACTIVE INGREDIENTS: WATER

Global Care Isopropyl Rubbing Alcohol

Active Ingredient

Isopropyl Alcohol 70%

Purpose

First aid antiseptic

USE

helps prevent the risk of infections in minor cuts, scrapes and burns

Warning

For external use only.

Flammable. keep away from fire or flame, heat, spark, electrical

USE ONLY IN A WELL-VENTILATED AREA, FUMES MAY BE HARMFUL

Ask doctor before use

for deep wounds, animal bites or serious burns

Whem using this product

- do not get in to eyes
- do not apply over large areas of the body
- do not use longer than 1 week

Stop use and ask doctor if

the condition persists or gets worse

Keep out of the reach of children.

If swallowed, get medical help or contact a Poison Control Center right away.

Directions

- clean affected areas
- apply 1 to 3 times daily

Inactive ingredient

Softened Water

Other information

- store at controlled room temperature
- will produce serius gastric disturbances if taken internally